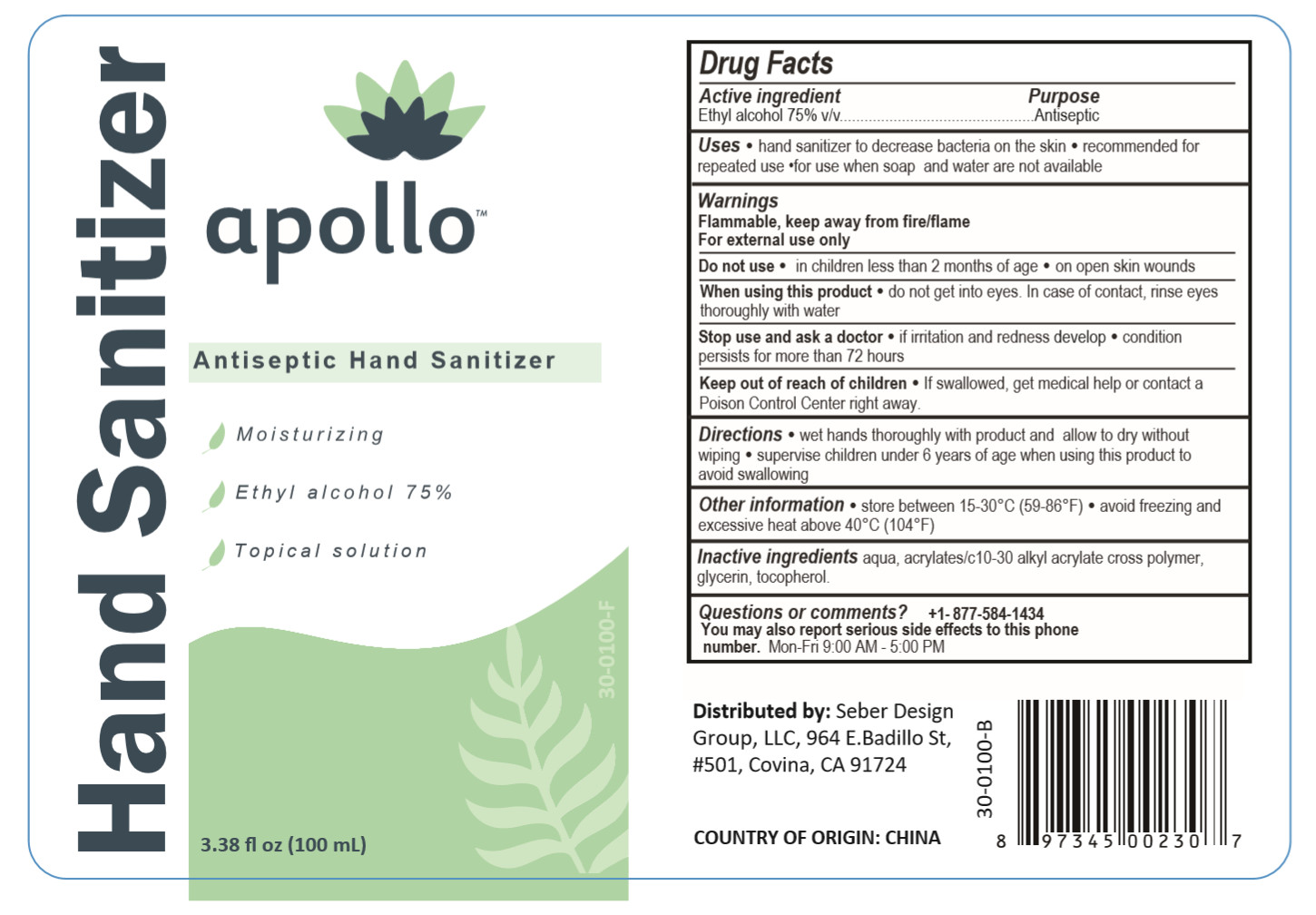 DRUG LABEL: Hand Sanitizer
NDC: 54237-009 | Form: LIQUID
Manufacturer: Guangzhou Daieme Cosmetic Co,.Ltd
Category: otc | Type: HUMAN OTC DRUG LABEL
Date: 20200518

ACTIVE INGREDIENTS: ALCOHOL 75 mL/100 mL
INACTIVE INGREDIENTS: CARBOMER INTERPOLYMER TYPE A (55000 CPS); GLYCERIN; TOCOPHEROL; WATER; ALOE

DOSAGE AND ADMINISTRATION

store between 15-30°C (59 86°F),avoid freezing and excessive heat above 40°C (104°F)

INACTIVE INGREDIENT

Acrylates/C10-30 Alkyl acrylate Crosspolymer, Aloe Extract,Glycerin,Tocopherol,Water

INDICATIONS AND USAGE

wet hands thoroughly with product and allow to dry without wiping

ACTIVE INGREDIENT

Alcohol

keep out of reach of children

PURPOSE

Disinfection
Sterilization
No Rinseing

WARNINGS

Flammable, keep away from fire/flame,For external use only